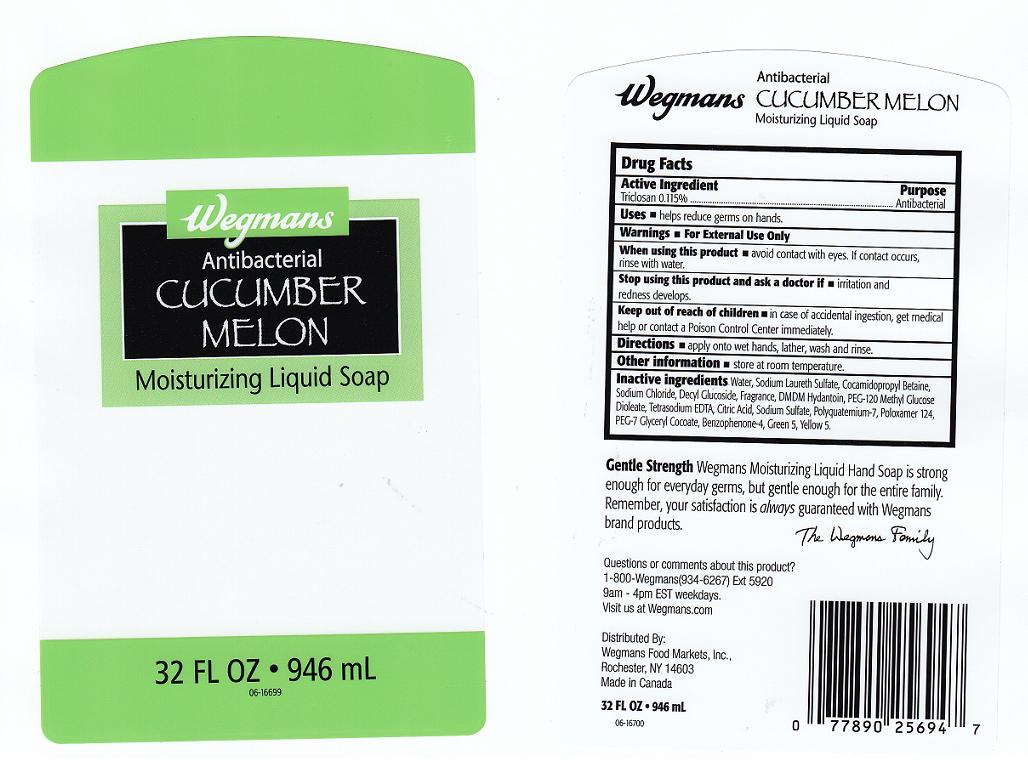 DRUG LABEL: ANTIBACTERIAL
NDC: 47124-295 | Form: LIQUID
Manufacturer: WEGMANS FOOD MARKETS INC
Category: otc | Type: HUMAN OTC DRUG LABEL
Date: 20110615

ACTIVE INGREDIENTS: TRICLOSAN 0.115 mL/100 mL
INACTIVE INGREDIENTS: WATER; SODIUM LAURETH SULFATE; COCAMIDOPROPYL BETAINE; SODIUM CHLORIDE; DECYL GLUCOSIDE; DMDM HYDANTOIN; PEG-120 METHYL GLUCOSE DIOLEATE; EDETATE SODIUM; CITRIC ACID MONOHYDRATE; SODIUM SULFATE; POLYQUATERNIUM-7 (70/30 ACRYLAMIDE/DADMAC; 1600 KD); POLOXAMER 124; PEG-7 GLYCERYL COCOATE; SULISOBENZONE; D&C GREEN NO. 5; FD&C YELLOW NO. 5

DRUG FACTS

ACTIVE INGREDIENT

TRICLOSAN 0.115%

PURPOSE

ANTIBACTERIAL

USES

HELPS REDUCE GERMS ON HANDS

WARNINGS

FOR EXTERNAL USE ONLY.

WHEN USING THIS PRODUCT

AVOID CONTACT WITH EYES. IF CONTACT OCCURS, RINSE WITH WATER.

STOP USING THIS PRODUCT AND ASK A DOCTOR IF

IRRITATION AND REDNESS DEVELOPS.

KEEP OUT REACH OF CHILDREN

IN CASE OF ACCIDENTAL INGESTION, GET MEDICAL HELP OR CONTACT A POISON CONTROL CENTER IMMEDIATELY.

DIRECTIONS

APPLY ONTO WET HANDS, LATHER, WASH AND RINSE.

OTHER INFORMATION

STORE AT ROOM TEMPERATURE.

INACTIVE INGREDIENTS

WATER, SODIUM LAURETH SULFATE, COCAMIDOPROPYL BETAINE, SODIUM CHLORIDE, DECYL GLUCOSIDE, FRAGRANCE, DMDM HYDANTOIN, PEG-120 METHYL GLUCOSE DIOLEATE, TETRASODIUM EDTA, CITRIC ACID, SODIUM SULFATE, POLYQUATERNIUM-7, PEG-7 GLYCERYL COCOATE, BENZOPHENONE-4, GREEN 5 (CI 61570), YELLOW 5 (CI 19140).